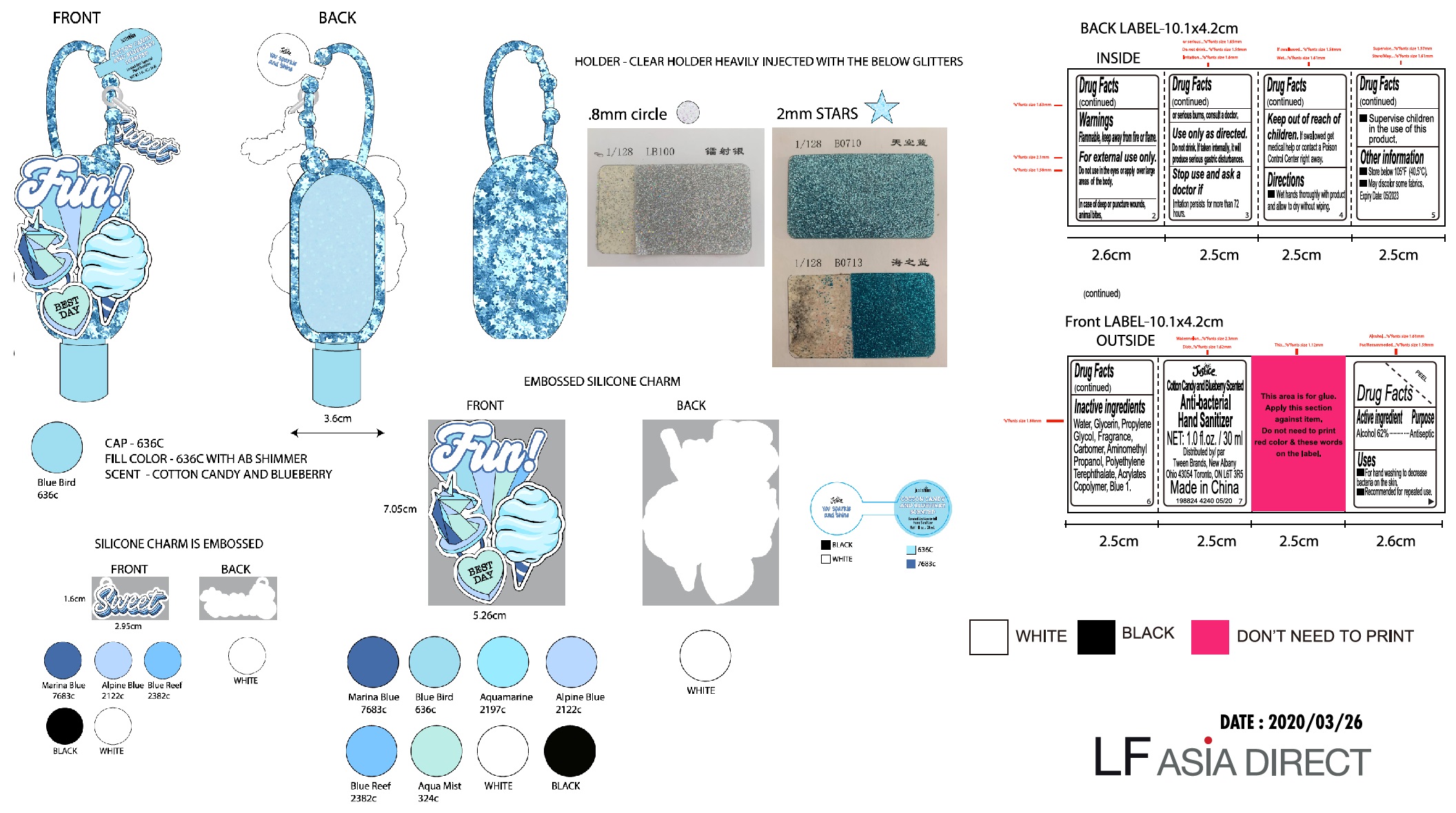 DRUG LABEL: Justice 198824 You Rock Antibacterial Cotton Candy Blueberry Hand Sanitizer
NDC: 60637-302 | Form: GEL
Manufacturer: Tween Brands,Inc.
Category: otc | Type: HUMAN OTC DRUG LABEL
Date: 20231025

ACTIVE INGREDIENTS: ALCOHOL 0.62 mL/1 mL
INACTIVE INGREDIENTS: WATER; GLYCERIN; PROPYLENE GLYCOL; CARBOMER HOMOPOLYMER, UNSPECIFIED TYPE; AMINOMETHYLPROPANOL; BUTYL ACRYLATE/METHYL METHACRYLATE/METHACRYLIC ACID COPOLYMER (18000 MW); FD&C BLUE NO. 1

Justice 198824 You Rock Antibacterial Cotton Candy Blueberry Hand Sanitizer

Active ingredient

Alcohol 62%

Purpose

Antiseptic

Use

- For hand washing to decrease bacteria on the skin.
- Recommended for repeated use.

Warnings

Flammable, keep away from fire or flames.

For external use only.

Do not use

in the eyes or apply over large areas of the body.

In case of deep or puncture wounds. animal bites, or serious burns, consult a doctor.

Use only as directed.

Do not drink. If taken internally, it will produce serious gastric disturbances.

Stop use and ask a doctor if

irritation persists for more than 72 hours.

Keep out of reach of children.

if swallowed get medical help or contact a Poison Control Center right away.

Directions

- wet hands thoroughly with product and allow to dry without wiping
- Supervise children in the use of this product.

Other information

Store below 105°F (40.5°C).

May discolor some fabrics.

Expiry Date: 05/2023

Inactive ingredients

Water, Glycerin, Propylene Glycol, Fragrance, Carbomer, Aminomethyl Propanol, Polyethylene Terephthalate, Acrylates Copolymer, Blue 1.